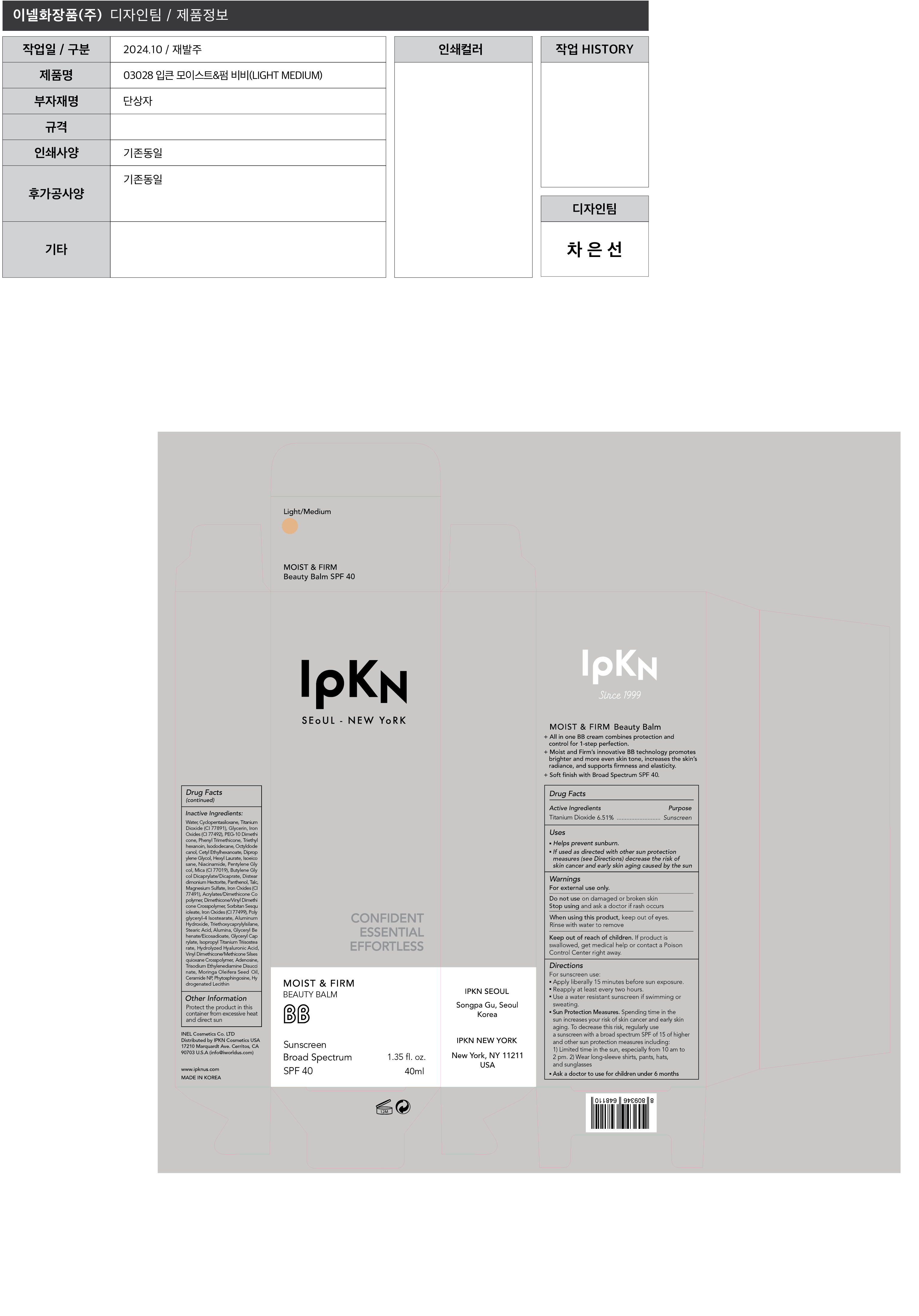 DRUG LABEL: IPKN Moist and Firm Beauty Balm Light Medium
NDC: 43526-129 | Form: CREAM
Manufacturer: Inel Cosmetics Co., Ltd.
Category: otc | Type: HUMAN OTC DRUG LABEL
Date: 20241025

ACTIVE INGREDIENTS: TITANIUM DIOXIDE 65.1 mg/1 mL
INACTIVE INGREDIENTS: HEXYL LAURATE; ISOEICOSANE; NIACINAMIDE; PENTYLENE GLYCOL; MICA; BUTYLENE GLYCOL DICAPRYLATE/DICAPRATE; DISTEARDIMONIUM HECTORITE; PANTHENOL; TALC; MAGNESIUM SULFATE, UNSPECIFIED FORM; FERRIC OXIDE RED; 2-ETHYLHEXYL ACRYLATE, METHACRYLATE, METHYL METHACRYLATE, OR BUTYL METHACRYLATE/HYDROXYPROPYL DIMETHICONE COPOLYMER (30000-300000 MW); DIMETHICONE/VINYL DIMETHICONE CROSSPOLYMER (HARD PARTICLE); SORBITAN SESQUIOLEATE; FERROSOFERRIC OXIDE; POLYGLYCERYL-4 ISOSTEARATE; ALUMINUM HYDROXIDE; TRIETHOXYCAPRYLYLSILANE; STEARIC ACID; ALUMINUM OXIDE; GLYCERYL BEHENATE/EICOSADIOATE; GLYCERYL MONOCAPRYLATE; ISOPROPYL TITANIUM TRIISOSTEARATE; HYALURONIC ACID; VINYL DIMETHICONE/METHICONE SILSESQUIOXANE CROSSPOLYMER; ADENOSINE; TRISODIUM ETHYLENEDIAMINE DISUCCINATE; MORINGA OLEIFERA SEED OIL; CERAMIDE NP; PHYTOSPHINGOSINE; HYDROGENATED SOYBEAN LECITHIN; WATER; CYCLOMETHICONE 5; GLYCERIN; FERRIC OXIDE YELLOW; PEG-10 DIMETHICONE (200 CST); PHENYL TRIMETHICONE; TRIETHYLHEXANOIN; ISODODECANE; OCTYLDODECANOL; CETYL ETHYLHEXANOATE; DIPROPYLENE GLYCOL

43526-129_IPKN Moist and Firm Beauty Balm Light Medium

ACTIVE INGREDIENT

Titanium Dioxide 6.51%

PURPOSE

Sunscreen

INDICATIONS AND USAGE

 Helps prevent sunburn
 If used as directed with other sun protection measures (see Directions) decrease the risk of skin cancer and early skin aging caused by the sun

DOSAGE AND ADMINISTRATION

For sunscreen use:
 Apply liberally 15 minutes before sun exposure
 Reapply at least every two hours
 Use a water-resistant sunscreen if swimming or sweating
 Sun protection measures. Spending time in the sun increases your risk of skin cancer and early skin aging. To decrease this risk, regularly use a sunscreen with a broad spectrum SPF of 15 of higher and other sun protection measures including: 1) Limited time in the sun, especially from 10 am to 2 pm. 2) Wear long-sleeve shirts, pants, hats, and sunglasses
 Ask a doctor to use for children under 6 months

WARNINGS

 For external use only
 Do not use on damaged or broken skin
 Stop using and ask a doctor if rash occurs
 When using this product, keep out of eyes. Rinse with water to remove
 Keep out of reach of children. If product is swallowed, get medical help or contact a Poison Control Center right away

KEEP OUT OF REACH OF CHILDREN

Keep out of reach of the children. If product is swallowed, get medical help or contact a poison control center right away.

INACTIVE INGREDIENT

Water, Cyclopentasiloxane, Titanium Dioxide (CI 77891), Glycerin, Iron Oxides (CI 77492), PEG-10 Dimethicone, Phenyl Trimethicone, Triethylhexanoin, Isododecane, Octyldodecanol, Cetyl Ethylhexanoate, Dipropylene Glycol, Hexyl Laurate, Isoeicosane, Niacinamide, Pentylene Glycol, Mica (CI 77019), Butylene Glycol Dicaprylate/Dicaprate, Disteardimonium Hectorite, Panthenol, Talc, Magnesium Sulfate, Iron Oxides (CI 77491), Acrylates/Dimethicone Copolymer, Dimethicone/Vinyl Dimethicone Crosspolymer, Sorbitan Sesquioleate, Iron Oxides (CI 77499), Polyglyceryl-4 Isostearate, Aluminum Hydroxide, Triethoxycaprylylsilane, Stearic Acid, Alumina, Glyceryl Behenate/Eicosadioate, Glyceryl Caprylate, Isopropyl Titanium Triisostearate, Hydrolyzed Hyaluronic Acid, Vinyl Dimethicone/Methicone Silsesquioxane Crosspolymer, Adenosine, Trisodium Ethylenediamine Disuccinate, Moringa Oleifera Seed Oil, Ceramide NP, Phytosphingosine, Hydrogenated Lecithin